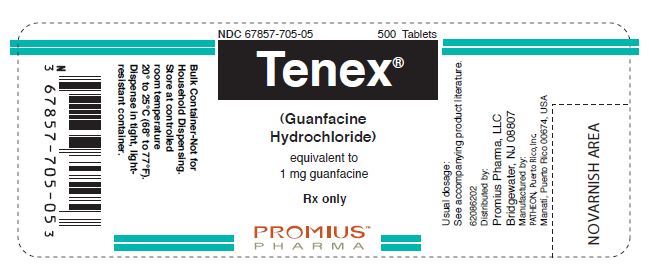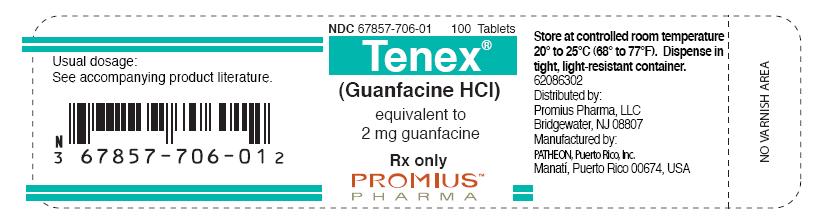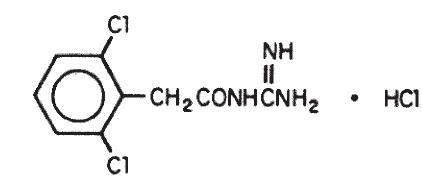 DRUG LABEL: TENEX 
NDC: 67857-705 | Form: TABLET
Manufacturer: Promius Pharma, LLC
Category: prescription | Type: HUMAN PRESCRIPTION DRUG LABEL
Date: 20130508

ACTIVE INGREDIENTS: GUANFACINE HYDROCHLORIDE 1 mg/1 1
INACTIVE INGREDIENTS: FD&C RED NO. 40; ANHYDROUS LACTOSE; CELLULOSE, MICROCRYSTALLINE; POVIDONE; STEARIC ACID

DESCRIPTION

Tenex (guanfacine hydrochloride) is a centrally acting antihypertensive with α2-adrenoceptor agonist properties in tablet form for oral administration.

The chemical name of Tenex (guanfacine hydrochloride) is N-amidino- 2-(2,6-dichlorophenyl) acetamide hydrochloride and its molecular weight is 282.56. Its structural formula is:

Guanfacine hydrochloride is a white to off-white powder; sparingly soluble in water and alcohol and slightly soluble in acetone. The tablets contain the following inactive ingredients:

1 mg—FD&C Red 40 aluminum lake, lactose, microcrystalline cellulose, povidone, stearic acid.

2 mg—D&C Yellow 10 aluminum lake, lactose, microcrystalline cellulose, povidone, stearic acid.

CLINICAL PHARMACOLOGY

Tenex (guanfacine hydrochloride) is an orally active antihypertensive agent whose principal mechanism of action appears to be stimulation of central α2-adrenergic receptors. By stimulating these receptors, guanfacine reduces sympathetic nerve impulses from the vasomotor center to the heart and blood vessels. This results in a decrease in peripheral vascular resistance and a reduction in heart rate.

The dose-response relationship for blood pressure and adverse effects of guanfacine given once a day as monotherapy has been evaluated in patients with mild to moderate hypertension. In this study patients were randomized to placebo or to 0.5 mg, 1 mg, 2 mg, 3 mg, or 5 mg of Tenex. Results are shown in the following table. A useful effect was not observed overall until doses of 2 mg were reached, although responses in white patients were seen at 1 mg; 24 hour effectiveness of 1 mg to 3 mg doses was documented using 24 hour ambulatory monitoring. While the 5 mg dose added an increment of effectiveness, it caused an unacceptable increase in adverse reactions.

Mean Changes (mm Hg) from Baseline in Seated Systolic and Diastolic Blood Pressure for Patients Completing 4 to 8 Weeks of Treatment with Guanfacine Monotherapy
Mean Change S/D [S/D = Systolic/diastolic blood pressure] Seated | n = (range) | Placebo | 0.5 mg | 1 mg | 2 mg | 3 mg | 5 mg
White Patients | 11–30 | -1/-5 | -6/-8 | -8/-9 | -12/-11 | -15/-12 | -18/-16
Black Patients | 8–28 | -3/-5 | 0/-2 | -3/-5 | -7/-7 | -8/-9 | -19/-15

Controlled clinical trials in patients with mild to moderate hypertension who were receiving a thiazide-type diuretic have defined the dose-response relationship for blood pressure response and adverse reactions of guanfacine given at bedtime and have shown that the blood pressure response to guanfacine can persist for 24 hours after a single dose. In the 12-week placebo-controlled dose-response study, patients were randomized to placebo or to doses of 0.5, 1, 2, and 3 mg of guanfacine, in addition to 25 mg chlorthalidone, each given at bedtime. The observed mean changes from baseline, tabulated below, indicate the similarity of response for placebo and the 0.5 mg dose. Doses of 1, 2, and 3 mg resulted in decreased blood pressure in the sitting position with no real differences among the three doses. In the standing position, there was some increase in response with dose.

Mean Decreases (mm Hg) in Seated and Standing Blood Pressure for Patients Treated with Guanfacine in Combination with Chlorthalidone
Mean Change | n = | Placebo 63 | 0.5 mg 63 | 1 mg 64 | 2 mg 58 | 3 mg 59
SD [S/D = Systolic/diastolic blood pressure] Seated |  | -5/-7 | -5/-6 | -14/-13 | -12/-13 | -16/-13
SD Standing |  | -3/-5 | -5/-4 | -11/-9 | -9/-10 | -15/-12

While most of the effectiveness of guanfacine in combination (and as monotherapy in white patients) was present at 1 mg, adverse reactions at this dose were not clearly distinguishable from those associated with placebo. Adverse reactions were clearly present at 2 and 3 mg (see ADVERSE REACTIONS).

In a second 12-week placebo-controlled study of 1, 2 or 3 mg of Tenex (guanfacine hydrochloride) administered with 25 mg of chlorthalidone once daily, a significant decrease in blood pressure was maintained for a full 24 hours after dosing. While there was no significant difference between the 12 and 24 hour blood pressure readings, the fall in blood pressure at 24 hours was numerically smaller, suggesting possible escape of blood pressure in some patients and the need for individualization of therapy.

In a double-blind, randomized trial, either guanfacine or clonidine was given at recommended doses with 25 mg chlorthalidone for 24 weeks and then abruptly discontinued. Results showed equal degrees of blood pressure reduction with the two drugs and there was no tendency for blood pressures to increase despite maintenance of the same daily dose of the two drugs. Signs and symptoms of rebound phenomena were infrequent upon discontinuation of either drug. Abrupt withdrawal of clonidine produced a rapid return of diastolic and especially systolic blood pressure to approximately pretreatment levels, with occasional values significantly greater than baseline, whereas guanfacine withdrawal produced a more gradual increase to pretreatment levels, but also with occasional values significantly greater than baseline.

Pharmacodynamics

Hemodynamic studies in man showed that the decrease in blood pressure observed after single-dose or long-term oral treatment with guanfacine was accompanied by a significant decrease in peripheral resistance and a slight reduction in heart rate (5 beats/min). Cardiac output under conditions of rest or exercise was not altered by guanfacine.

Tenex (guanfacine hydrochloride) lowered elevated plasma renin activity and plasma catecholamine levels in hypertensive patients, but this does not correlate with individual blood-pressure responses.

Growth hormone secretion was stimulated with single oral doses of 2 and 4 mg of guanfacine. Long-term use of Tenex had no effect on growth hormone levels.

Guanfacine had no effect on plasma aldosterone. A slight but insignificant decrease in plasma volume occurred after one month of guanfacine therapy. There were no changes in mean body weight or electrolytes.

Pharmacokinetics

Relative to an intravenous dose of 3 mg, the absolute oral bioavailability of guanfacine is about 80%. Peak plasma concentrations occur from 1 to 4 hours with an average of 2.6 hours after single oral doses or at steady state.

The area under the concentration-time curve (AUC) increases linearly with the dose.

In individuals with normal renal function, the average elimination half-life is approximately 17 hr (range 10 - 30 hr). Younger patients tend to have shorter elimination half-lives (13 - 14 hr) while older patients tend to have half-lives at the upper end of the range. Steady state blood levels were attained within 4 days in most subjects.

In individuals with normal renal function, guanfacine and its metabolites are excreted primarily in the urine. Approximately 50% (40 - 75%) of the dose is eliminated in the urine as unchanged drug; the remainder is eliminated mostly as conjugates of metabolites produced by oxidative metabolism of the aromatic ring.

The guanfacine-to-creatinine clearance ratio is greater than 1.0, which would suggest that tubular secretion of drug occurs.

The drug is approximately 70% bound to plasma proteins, independent of drug concentration.

The whole body volume of distribution is high (a mean of 6.3 L/kg), which suggests a high distribution of drug to the tissues.

The clearance of guanfacine in patients with varying degrees of renal insufficiency is reduced, but plasma levels of drug are only slightly increased compared to patients with normal renal function. When prescribing for patients with renal impairment, the low end of the dosing range should be used. Patients on dialysis also can be given usual doses of guanfacine hydrochloride as the drug is poorly dialyzed.

INDICATIONS AND USAGE

Tenex (guanfacine hydrochloride) is indicated in the management of hypertension. Tenex may be given alone or in combination with other antihypertensive agents, especially thiazide-type diuretics.

CONTRAINDICATIONS

Tenex is contraindicated in patients with known hypersensitivity to guanfacine hydrochloride.

PRECAUTIONS

General

Like other antihypertensive agents, Tenex (guanfacine hydrochloride) should be used with caution in patients with severe coronary insufficiency, recent myocardial infarction, cerebrovascular disease, or chronic renal or hepatic failure.

Sedation

Tenex, like other orally active central α2-adrenergic agonists, causes sedation or drowsiness, especially when beginning therapy. These symptoms are dose-related (see ADVERSE REACTIONS). When Tenex is used with other centrally active depressants (such as phenothiazines, barbiturates, or benzodiazepines), the potential for additive sedative effects should be considered.

Rebound

Abrupt cessation of therapy with orally active central α2-adrenergic agonists may be associated with increases (from depressed on-therapy levels) in plasma and urinary catecholamines, symptoms of "nervousness and anxiety" and, less commonly, increases in blood pressure to levels significantly greater than those prior to therapy.

Information for Patients

Patients who receive Tenex should be advised to exercise caution when operating dangerous machinery or driving motor vehicles until it is determined that they do not become drowsy or dizzy from the medication. Patients should be warned that their tolerance for alcohol and other CNS depressants may be diminished. Patients should be advised not to discontinue therapy abruptly.

Laboratory Tests

In clinical trials, no clinically relevant laboratory test abnormalities were identified as causally related to drug during short-term treatment with Tenex (guanfancine hydrochloride).

Drug Interactions

The potential for increased sedation when Tenex is given with other CNS-depressant drugs should be appreciated.

The administration of guanfacine concomitantly with a known microsomal enzyme inducer (phenobarbital or phenytoin) to two patients with renal impairment reportedly resulted in significant reductions in elimination half-life and plasma concentration. In such cases, therefore, more frequent dosing may be required to achieve or maintain the desired hypotensive response. Further, if guanfacine is to be discontinued in such patients, careful tapering of the dosage may be necessary in order to avoid rebound phenomena (see Rebound above).

Anticoagulants

Ten patients who were stabilized on oral anticoagulants were given guanfacine, 1 - 2 mg/day, for 4 weeks. No changes were observed in the degree of anticoagulation.

In several well-controlled studies, guanfacine was administered together with diuretics with no drug interactions reported. In the long-term safety studies, Tenex was given concomitantly with many drugs without evidence of any interactions. The principal drugs given (number of patients in parentheses) were: cardiac glycosides (115), sedatives and hypnotics (103), coronary vasodilators (52), oral hypoglycemics (45), cough and cold preparations (45), NSAIDs (38), antihyperlipidemics (29), antigout drugs (24), oral contraceptives (18), bronchodilators (13), insulin (10), and beta blockers (10).

Drug/Laboratory Test Interactions

No laboratory test abnormalities related to the use of Tenex (guanfacine hydrochloride) have been identified.

Carcinogenesis, Mutagenesis, Impairment of Fertility

No carcinogenic effect was observed in studies of 78 weeks in mice at doses more than 150 times the maximum recommended human dose and 102 weeks in rats at doses more than 100 times the maximum recommended human dose. In a variety of test models, guanfacine was not mutagenic.

No adverse effects were observed in fertility studies in male and female rats.

Pregnancy Category B

Administration of guanfacine to rats at 70 times the maximum recommended human dose and to rabbits at 20 times the maximum recommended human dose resulted in no evidence of harm to the fetus. Higher doses (100 and 200 times the maximum recommended human dose in rabbits and rats respectively) were associated with reduced fetal survival and maternal toxicity. Rat experiments have shown that guanfacine crosses the placenta.

There are, however, no adequate and well-controlled studies in pregnant women. Because animal reproduction studies are not always predictive of human response, this drug should be used during pregnancy only if clearly needed.

PREGNANCY

Labor and Delivery

Tenex (guanfacine hydrochloride) is not recommended in the treatment of acute hypertension associated with toxemia of pregnancy. There is no information available on the effects of guanfacine on the course of labor and delivery.

Nursing Mothers

It is not known whether Tenex (guanfacine hydrochloride) is excreted in human milk. Because many drugs are excreted in human milk, caution should be exercised when Tenex is administered to a nursing woman. Experiments with rats have shown that guanfacine is excreted in the milk.

USE IN SPECIFIC POPULATIONS

Pediatric Use

Safety and effectiveness in children under 12 years of age have not been demonstrated. Therefore, the use of Tenex in this age group is not recommended. There have been spontaneous postmarketing reports of mania and aggressive behavioral changes in pediatric patients with attention-deficit hyperactivity disorder (ADHD) receiving Tenex. The reported cases were from a single center. All patients had medical or family risk factors for bipolar disorder. All patients recovered upon discontinuation of guanfacine HCl. Hallucinations have been reported in pediatric patients receiving Tenex for treatment of attention-deficit hyperactivity disorder.

Geriatric Use

Clinical studies of Tenex did not include sufficient numbers of subjects aged 65 and over to determine whether they responded differently from younger subjects. Other reported clinical experience has not identified differences in responses between the elderly and younger patients.

In general, dose selection for an elderly patient should be cautious, usually starting at the low end of the dosing range, reflecting the greater frequency of decreased hepatic, renal or cardiac function, and of concomitant disease or other drug therapy (see CLINICAL PHARMACOLOGY: Pharmacokinetics).

ADVERSE REACTIONS

Adverse reactions noted with Tenex (guanfacine hydrochloride) are similar to those of other drugs of the central α2-adrenoreceptor agonist class: dry mouth, sedation (somnolence), weakness (asthenia), dizziness, constipation, and impotence. While the reactions are common, most are mild and tend to disappear on continued dosing.

Skin rash with exfoliation has been reported in a few cases; although clear cause and effect relationships to Tenex could not be established, should a rash occur, Tenex should be discontinued and the patient monitored appropriately.

In the dose-response monotherapy study described under CLINICAL PHARMACOLOGY, the frequency of the most commonly observed adverse reactions showed a dose relationship from 0.5 to 3 mg as follows:

Adverse Reaction | Placebo n=59 | 0.5 mg n=60 | 1 mg n=61 | 2 mg n=60 | 3 mg n=59
Dry Mouth | 0% | 10% | 10% | 42% | 54%
Somnolence | 8% | 5% | 10% | 13% | 39%
Asthenia | 0% | 2% | 3% | 7% | 3%
Dizziness | 8% | 12% | 2% | 8% | 15%
Headache | 8% | 13% | 7% | 5% | 3%
Impotence | 0% | 0% | 0% | 7% | 3%
Constipation | 0% | 2% | 0% | 5% | 15%
Fatigue | 2% | 2% | 5% | 8% | 10%

The percent of patients who dropped out because of adverse reactions are shown below for each dosage group.

 | Placebo | 0.5 mg | 1 mg | 2 mg | 3 mg
Percent dropouts | 0% | 2.0% | 5.0% | 13% | 32%

The most common reasons for dropouts among patients who received guanfacine were dry mouth, somnolence, dizziness, fatigue, weakness, and constipation.

In the 12-week, placebo-controlled, dose-response study of guanfacine administered with 25 mg chlorthalidone at bedtime, the frequency of the most commonly observed adverse reactions showed a clear dose relationship from 0.5 to 3 mg as follows:

Adverse Reaction | Placebo n=73 | 0.5 mg n=72 | 1 mg n=72 | 2 mg n=72 | 3 mg n=72
Dry Mouth | 5 (7%) | 4 (5%) | 6 (8%) | 8 (11%) | 20 (28%)
Somnolence | 1 (1%) | 3 (4%) | 0 (0%) | 1 (1%) | 10 (14%)
Asthenia | 0 (0%) | 2 (3%) | 0 (0%) | 2 (2%) | 7 (10%)
Dizziness | 2 (2%) | 1 (1%) | 3 (4%) | 6 (8%) | 3 (4%)
Headache | 3 (4%) | 4 (3%) | 3 (4%) | 1 (1%) | 2 (2%)
Impotence | 1 (1%) | 1 (0%) | 0 (0%) | 1 (1%) | 3 (4%)
Constipation | 0 (0%) | 0 (0%) | 0 (0%) | 1 (1%) | 1 (1%)
Fatigue | 3 (3%) | 2 (3%) | 2 (3%) | 5 (6%) | 3 (4%)

There were 41 premature terminations because of adverse reactions in this study. The percent of patients who dropped out and the dose at which the dropout occurred were as follows:

Dose | Placebo | 0.5 mg | 1 mg | 2 mg | 3 mg
Percent dropouts | 6.9% | 4.2% | 3.2% | 6.9% | 8.3%

Reasons for dropouts among patients who received guanfacine were: somnolence, headache, weakness, dry mouth, dizziness, impotence, insomnia, constipation, syncope, urinary incontinence, conjunctivitis, paresthesia, and dermatitis.

In a second 12-week placebo-controlled combination therapy study in which the dose could be adjusted upward to 3 mg per day in 1-mg increments at 3-week intervals, i.e., a setting more similar to ordinary clinical use, the most commonly recorded reactions were: dry mouth, 47%; constipation, 16%; fatigue, 12%; somnolence, 10%; asthenia, 6%; dizziness, 6%; headache, 4%; and insomnia, 4%.

Reasons for dropouts among patients who received guanfacine were: somnolence, dry mouth, dizziness, impotence, constipation, confusion, depression, and palpitations.

In the clonidine/guanfacine comparison described in CLINICAL PHARMACOLOGY, the most common adverse reactions noted were as follows:

Adverse Reactions | Guanfacine (n=279) | Clonidine (n=278)
Dry Mouth | 30% | 37%
Somnolence | 21% | 35%
Dizziness | 11% | 8%
Constipation | 10% | 5%
Fatigue | 9% | 8%
Headache | 4% | 4%
Insomnia | 4% | 3%

Adverse reactions occurring in 3% or less of patients in the three controlled trials of Tenex (guanfacine hydrochloride) with a diuretic were:

Cardiovascular- bradycardia, palpitations, substernal pain

Gastrointestinal- abdominal pain, diarrhea, dyspepsia, dysphagia, nausea

CNS- amnesia, confusion, depression, insomnia, libido decrease

ENT disorders- rhinitis, taste perversion, tinnitus

Eye disorders- conjunctivitis, iritis, vision disturbance

Musculoskeletal- leg cramps, hypokinesia

Respiratory- dyspnea

Dermatologic- dermatitis, pruritus, purpura, sweating

Urogenital- testicular disorder, urinary incontinence

Other- malaise, paresthesia, paresis

Adverse reaction reports tend to decrease over time. In an open-label trial of one year's duration, 580 hypertensive subjects were given guanfacine, titrated to achieve goal blood pressure, alone (51%), with diuretic (38%), with beta blocker (3%), with diuretic plus beta blocker (6%), or with diuretic plus vasodilator (2%). The mean daily dose of guanfacine reached was 4.7 mg.

Adverse Reaction | Incidence of adverse reactions at any time during the study | Incidence of adverse reactions at end of one year
 | n = 580 | n = 580
Dry Mouth | 60% | 15%
Drowsiness | 33% | 6%
Dizziness | 15% | 1%
Constipation | 14% | 3%
Weakness | 5% | 1%
Headache | 4% | 0.2%
Insomnia | 5% | 0%

There were 52 (8.9%) dropouts due to adverse effects in this 1-year trial. The causes were: dry mouth (n = 20), weakness (n = 12), constipation (n = 7), somnolence (n = 3), nausea (n = 3), orthostatic hypotension (n = 2), insomnia (n = 1), rash (n = 1), nightmares (n = 1), headache (n = 1), and depression (n = 1).

Postmarketing Experience

An open-label postmarketing study involving 21,718 patients was conducted to assess the safety of Tenex (guanfacine hydrochloride) 1 mg/day given at bedtime for 28 days. Tenex was administered with or without other antihypertensive agents. Adverse events reported in the postmarketing study at an incidence greater than 1% included dry mouth, dizziness, somnolence, fatigue, headache and nausea. The most commonly reported adverse events in this study were the same as those observed in controlled clinical trials.

Less frequent, possibly Tenex-related events observed in the postmarketing study and/or reported spontaneously include:

BODY AS A WHOLE asthenia, chest pain, edema, malaise, tremor

CARDIOVASCULAR bradycardia, palpitations, syncope, tachycardia

CENTRAL NERVOUS SYSTEM paresthesias, vertigo

EYE DISORDERS blurred vision

GASTROINTESTINAL SYSTEM abdominal pain, constipation, diarrhea, dyspepsia

LIVER AND BILLIARY SYSTEM abnormal liver function tests

MUSCULO-SKELETAL SYSTEM arthralgia, leg cramps, leg pain, myalgia

PSYCHIATRIC agitation, anxiety, confusion, depression, insomnia, nervousness

RREPRODUCTIVE SYSTEM, Male- impotence

RESPIRATORY SYSTEM dyspnea

SKIN AND APPENDAGES alopecia, dermatitis, exfoliative dermatitis, pruritus, rash

SPECIAL SENSES alterations in taste

URINARY SYSTEM nocturia, urinary frequency

Rare, serious disorders with no definitive cause and effect relationship to Tenex have been reported spontaneously and/or in the postmarketing study. These events include acute renal failure, cardiac fibrillation, cerebrovascular accident, congestive heart failure, heart block, and myocardial infarction.

DRUG ABUSE AND DEPENDENCE

No reported abuse or dependence has been associated with the administration of Tenex (guanfacine hdyrochloride).

OVERDOSAGE

Signs and Symptoms

Drowsiness, lethargy, bradycardia and hypotension have been observed following overdose with guanfacine.

A 25-year-old female intentionally ingested 60 mg. She presented with severe drowsiness and bradycardia of 45 beats/minute. Gastric lavage was performed and an infusion of isoproterenol (0.8 mg in 12 hours) was administered. She recovered quickly and without sequelae.

A 28-year-old female who ingested 30 - 40 mg developed only lethargy, was treated with activated charcoal and a cathartic, was monitored for 24 hours, and was discharged in good health.

A 2-year-old male weighing 12 kg who ingested up to 4 mg of guanfacine developed lethargy. Gastric lavage (followed by activated charcoal and sorbitol slurry via NG tube) removed some tablet fragments within 2 hours after ingestion, and vital signs were normal.

During 24-hour observation in ICU, systolic pressure was 58 and heart rate 70 at 16 hours post-ingestion. No intervention was required, and child was discharged fully recovered the next day.

Treatment of Overdosage

Gastric lavage and supportive therapy as appropriate. Guanfacine is not dialyzable in clinically significant amounts (2.4%).

DOSAGE AND ADMINISTRATION

The recommended initial dose of Tenex (guanfacine hydrochloride) when given alone or in combination with another antihypertensive drug is 1 mg daily given at bedtime to minimize somnolence. If after 3 to 4 weeks of therapy 1 mg does not give a satisfactory result, a dose of 2 mg may be given, although most of the effect of Tenex is seen at 1 mg (see CLINICAL PHARMACOLOGY). Higher daily doses have been used, but adverse reactions increase significantly with doses above 3 mg/day.

The frequency of rebound hypertension is low, but it can occur. When rebound occurs, it does so after 2 - 4 days, which is delayed compared with clonidine hydrochloride. This is consistent with the longer half-life of guanfacine. In most cases, after abrupt withdrawal of guanfacine, blood pressure returns to pretreatment levels slowly (within 2 - 4 days) without ill effects.

HOW SUPPLIED

Tenex® (guanfacine hydrochloride) Tablets are available in the following dosing strengths (expressed in equivalent amounts of guanfacine):

1 mg—light pink, diamond-shaped tablet embossed with a 1 and engraved RP on one side and engraved TENEX on the other side in bottles of 100 (NDC 67857-705-01) and 500 (NDC 67857-705-05).

2 mg—yellow, diamond-shaped tablet, one side engraved TENEX, other side engraved 2 with RP below it in bottles of 100 (NDC 67857-706-01).

Store at controlled temperature, between 20ଌ and 25°C (68°F and 77°F).

Dispense in a tight, light-resistant container.

Distributed by:
Promius Pharma, LLC
Bridgewater, NJ 08807

Manufactured by:
PATHEON, Puerto Rico, Inc.
Manati, Puerto Rico 00674, USA

Revised: May 2013

PACKAGE LABEL

NDC-67857-706-01 100 Tablets

TENEX®

(Guanfancine HCL)

equivalent to
2 mg guanfancine

Rx only

PROMIUS PHARMA

PACKAGE LABEL

NDC-67857-705-05 500 Tablets

TENEX®

(Guanfancine HCL)

equivalent to
1 mg guanfancine

Rx only

PROMIUS PHARMA